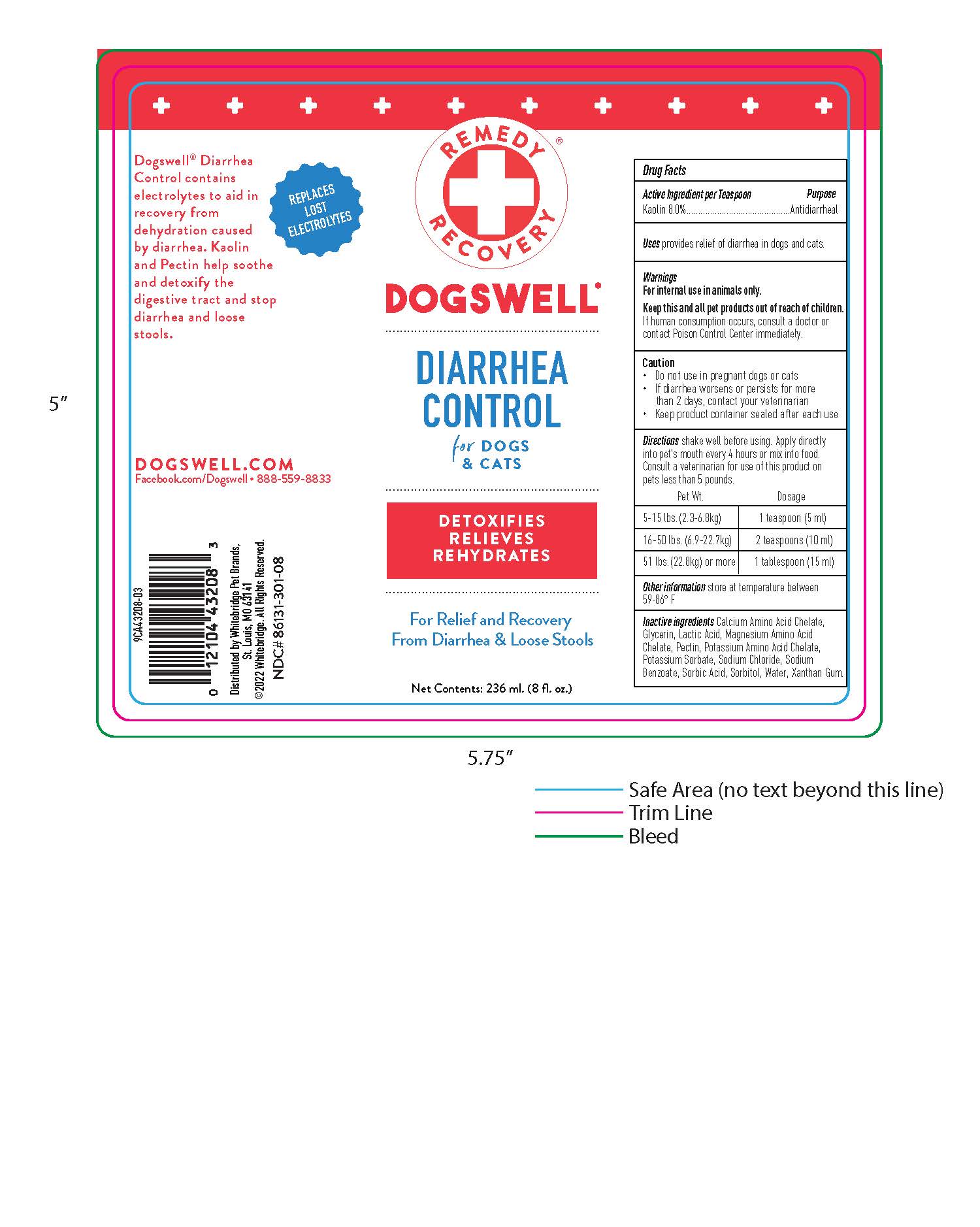 DRUG LABEL: Diarrhea Control
NDC: 86131-301 | Form: LIQUID
Manufacturer: Whitebridge Pet Brands
Category: animal | Type: OTC ANIMAL DRUG LABEL
Date: 20251223

ACTIVE INGREDIENTS: KAOLIN 8.0 mg/100 mL
INACTIVE INGREDIENTS: PECTIN; GLYCERIN; SORBIC ACID; XANTHAN GUM; SORBITOL; SODIUM BENZOATE; POTASSIUM SORBATE; POTASSIUM; CALCIUM; MAGNESIUM; SODIUM CHLORIDE; LACTIC ACID; WATER

DIARRHEA CONTROL

Active Ingredient per Teaspoon Purpose

Kaolin 8.0%..........Antidiarrheal

Uses

provides relief of diarrhea in dogs and cats.

Warnings

For internal use on animals only.

Keep this and all pet products out of reach of children.

If human consumption occurs, consult a doctor or contact Poison Control Center immediately.

Caution

- Do not use in pregnant dogs or cats
- If diarrhea worsens or persists for more than 2 days, contact your veterinarian
- Keep product container sealed after each use

Directions

shake well before using. Apply directly into pet's mouth every 4 hours or mix into food. Consult a veterinarian for use of this product on pets less than 5 pounds.

Pet Wt. | Dosage
5-10 lbs. (2.3-6.8kg) | 1 teaspoon (5ml)
16-50 lbs. (6.9-22.7kg) | 2 teaspoons (10ml)
51 lbs (22.8kg) or more | 1 tablespoon (15ml)

Other information

store at temperature between 59-86 F

Inactive ingredients

Calcium Amino Acid Chelate, Glycerin, Lactic Acid, Magnesium Amino Acid Chelate, Pectin, Potassium Amino Acid Chelate, Potassium Sorbate, Sodium Chloride, Sodium Benzoate, Sorbic Acid, Sorbitol, water, Xanthan Gum.

DESCRIPTION

REPLACES LOST ELECTROLYTES

Dogswell Diarrhea Control contains electrolytes to aid in recovery from dehydration caused by diarrhea. Kaolin and Pectin help soothe and detoxify the digestive tract and stop diarrhea and loose stools.

DOGSWELL.COM

Facebook.com/Dogswell 888-559-8833

Distributed by Whitebridge Pet Brands,

St. Louis, MO 63141

2022 Whitebridge. All Rights Reserved.

NDC# 86131-301-08

PACKAGE LABEL

REMEDY RECOVERY

DOGSWELL

DIARRHEA CONTROL

for DOGS & CATS

DETOXIFIES

RELIEVES

REHYRDATES

For Relief and Recovery

From Diarrhea & Loose Stools

Net Contents: 236 ml. (8 fl.oz.)